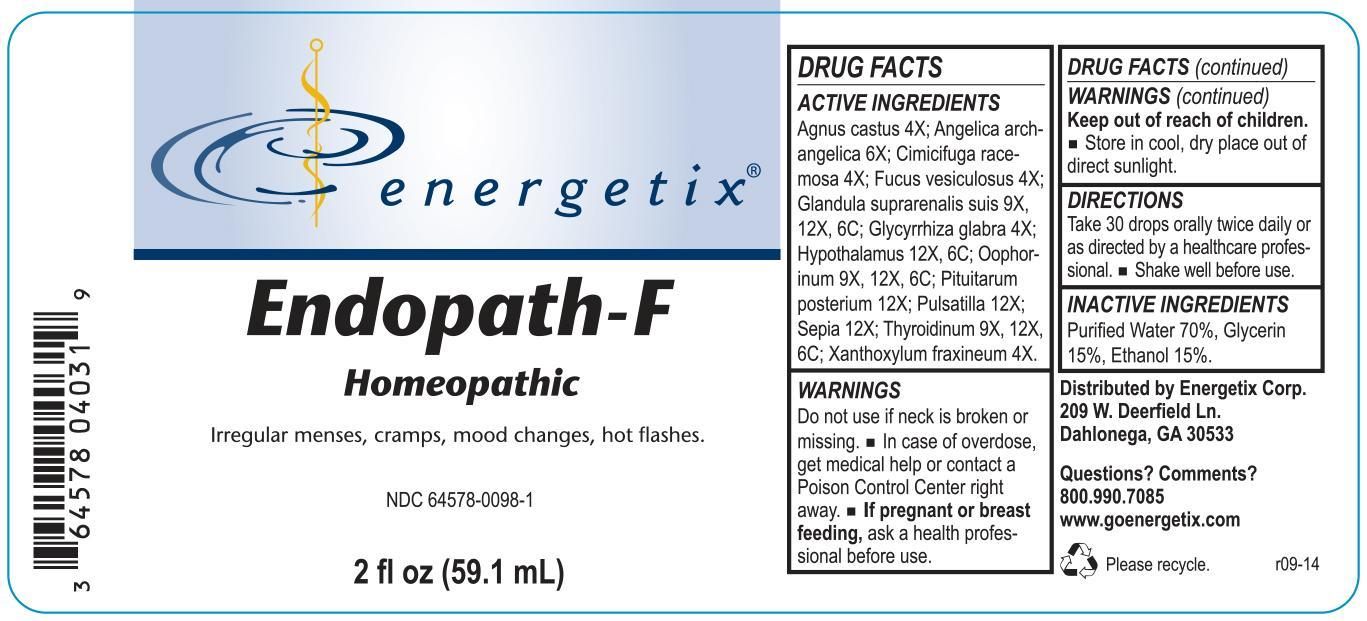 DRUG LABEL: Endopath-F
NDC: 64578-0098 | Form: LIQUID
Manufacturer: Energetix Corp
Category: homeopathic | Type: HUMAN OTC DRUG LABEL
Date: 20140402

ACTIVE INGREDIENTS: SUS SCROFA ADRENAL GLAND 9 [hp_X]/59.1 mL; CHASTE TREE 4 [hp_X]/59.1 mL; BLACK COHOSH 4 [hp_X]/59.1 mL; FUCUS VESICULOSUS 4 [hp_X]/59.1 mL; GLYCYRRHIZA GLABRA 4 [hp_X]/59.1 mL; BOS TAURUS HYPOTHALAMUS 12 [hp_X]/59.1 mL; ANGELICA ARCHANGELICA ROOT 6 [hp_X]/59.1 mL; SUS SCROFA OVARY 9 [hp_X]/59.1 mL; PULSATILLA VULGARIS 12 [hp_X]/59.1 mL; SEPIA OFFICINALIS JUICE 12 [hp_X]/59.1 mL; THYROID, UNSPECIFIED 9 [hp_X]/59.1 mL; ZANTHOXYLUM AMERICANUM BARK 4 [hp_X]/59.1 mL; SUS SCROFA PITUITARY GLAND 12 [hp_X]/59.1 mL
INACTIVE INGREDIENTS: ALCOHOL 8.862 mL/59.1 mL; GLYCERIN 8.862 mL/59.1 mL; WATER 41.356 mL/59.1 mL

Endopath-F

ACTIVE INGREDIENT

Agnus castus 4X; Angelica archangelica 6X; Cimicifuga racemosa 4X; Fucus vesiculosus 4X; Glandula suprarenalis suis 9X, 12X, 6C; Glycyrrhiza glabra 4X; Hypothalamus 12X, 6C; Oophorinum 9X, 12X, 6C; Pituitarum posterium 12X; Pulsatilla 12X; Sepia 12X; Thyroidinum 9X, 12X, 6C; Xanthoxylum fraxineum 4X.

Do not use if neck wrap is broken or missing.

OVERDOSAGE

In case of overdose, get medical help or contact a Poison Control Center right away.

PREGNANCY OR BREAST FEEDING

If pregnant or breast feeding, ask a health professional before use.

Keep out of reach of children.

STORAGE AND HANDLING

Store in cool, dry place out of direct sunlight.

Questions? Comments?
800.990.7085 www.goenergetix.com

PURPOSE

Irregular menses, cramps, mood changes, hot flashes.

INACTIVE INGREDIENT

Purified Water 70%, Glycerin 15%, Ethanol 15%.

DOSAGE AND ADMINISTRATION

Take 30 drops orally twice daily or as directed by a healthcare professional. Shake well before use.

INDICATIONS AND USAGE

Irregular menses, cramps, mood changes, hot flashes.